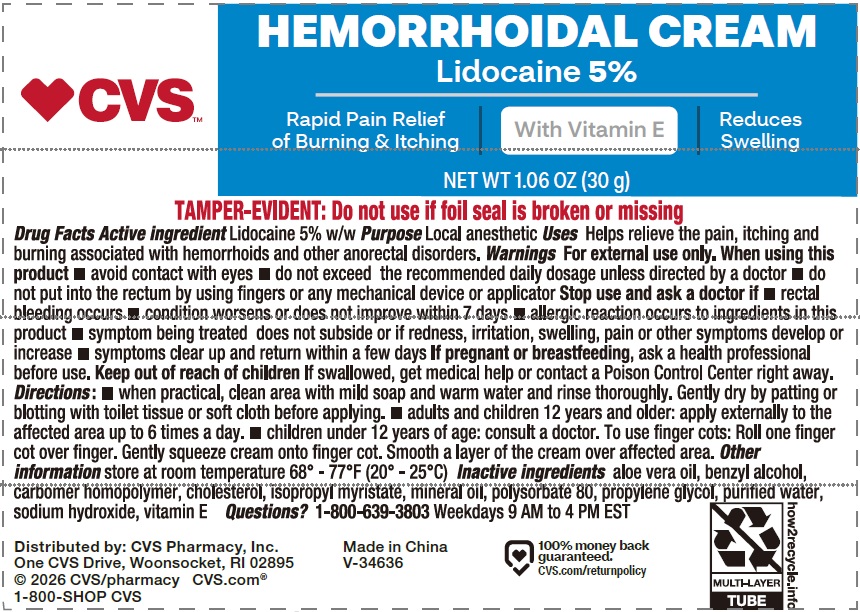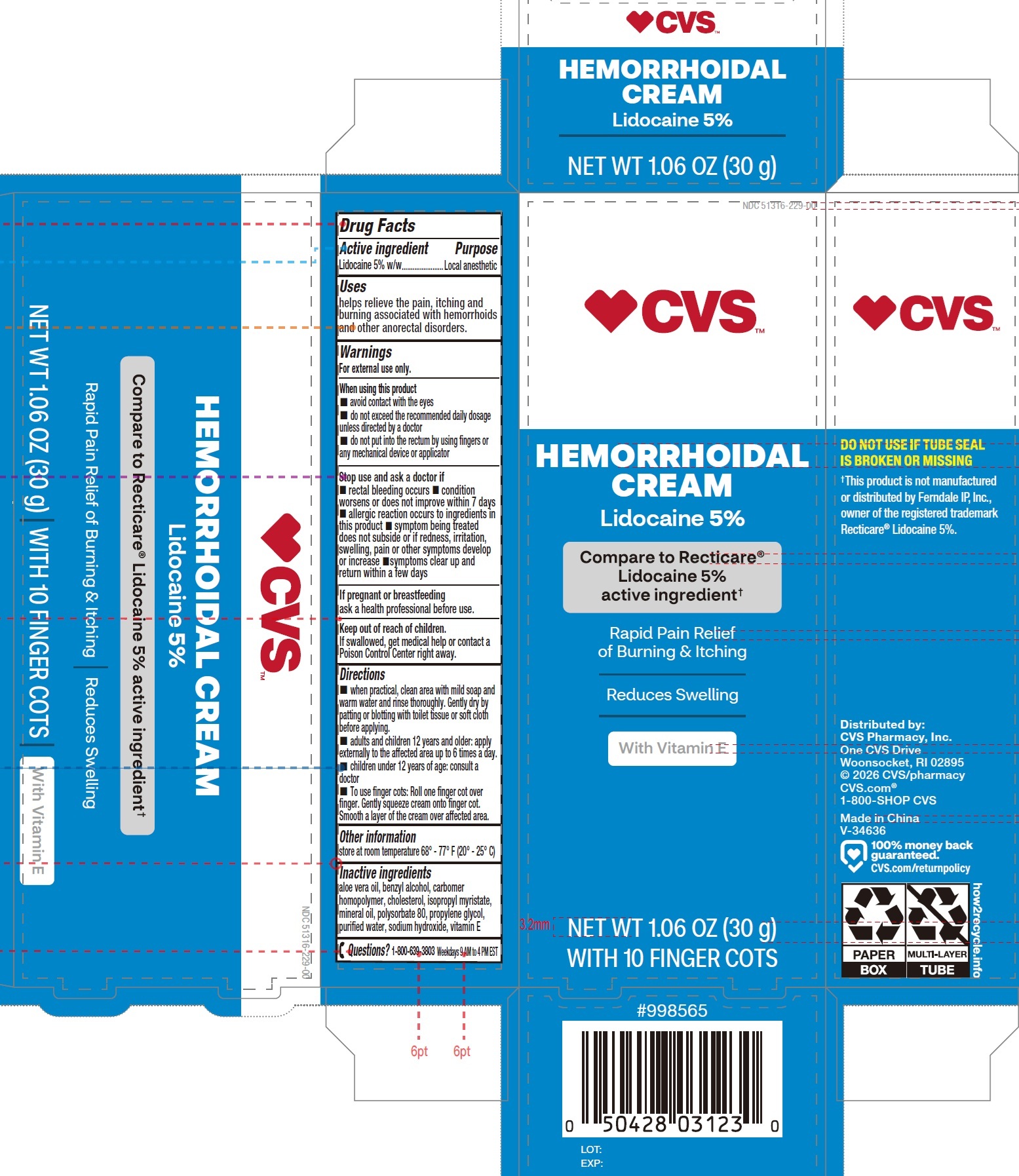 DRUG LABEL: CVS Hemorrhoidal Lidocaine 5 Rapid Pain Relief with 10 Finger Cots
NDC: 51316-204 | Form: KIT | Route: TOPICAL
Manufacturer: CVS PHARMACY, INC
Category: otc | Type: HUMAN OTC DRUG LABEL
Date: 20260105

ACTIVE INGREDIENTS: LIDOCAINE 50 mg/1 g
INACTIVE INGREDIENTS: BENZYL ALCOHOL; CARBOMER HOMOPOLYMER, UNSPECIFIED TYPE; CHOLESTEROL; ISOPROPYL MYRISTATE; MINERAL OIL; POLYSORBATE 80; PROPYLENE GLYCOL; WATER; SODIUM HYDROXIDE; .ALPHA.-TOCOPHEROL

CVS Hemorrhoidal Cream Lidocaine 5% Rapid Pain Relief with 10 Finger Cots

Active ingredient

Lidocaine 5% w/w

Purpose

Local anesthetic

Uses

helps relieve the pain, itching and burning associated with hemorrhoids and other anorectal disorders.

Warnings

For external use only.

When using this product

- avoid contact with the eyes
- do not exceed the recommended daily dosage unless directed by a doctor
- do not put into the rectum by using fingers or any mechanical device or applicator

Stop use and ask a doctor if

- rectal bleeding occurs
- condition worsens or does not improve within 7 days
- allergic reaction occurs to ingredients in this product
- symptom being treated does not subside or if redness, irritation, swelling, pain or other symptoms develop or increase
- symptoms clear up and return within a few days

If pregnant or breastfeeding

ask a health professional before use.

Keep out of reach of children.

If swallowed, get medical help or contact a Poison Control Center right away.

Directions

- when practical, clean area with mild soap and warm water and rinse thoroughly. Gently dry by patting or blotting with toilet tissue or soft cloth before applying.
- adults and children 12 years and older: apply externally to the affected area up to 6 times a day.
- children under 12 years of age: consult a doctor
- To use finger cots: Roll one finger cot over finger. Gently squeeze cream onto finger cot. Smooth a layer of the cream over affected area.

Other information

store at room temperature 68° - 77° F (20° - 25° C)

Inactive ingredients

aloe vera oil, benzyl alcohol, carbomer homopolymer, cholesterol, isopropyl myristate, mineral oil, polysorbate 80, propylene glycol, purified water, sodium hydroxide, vitamin E

Questions?

1-800-639-3803Weekdays 9 AM to 4 PM EST